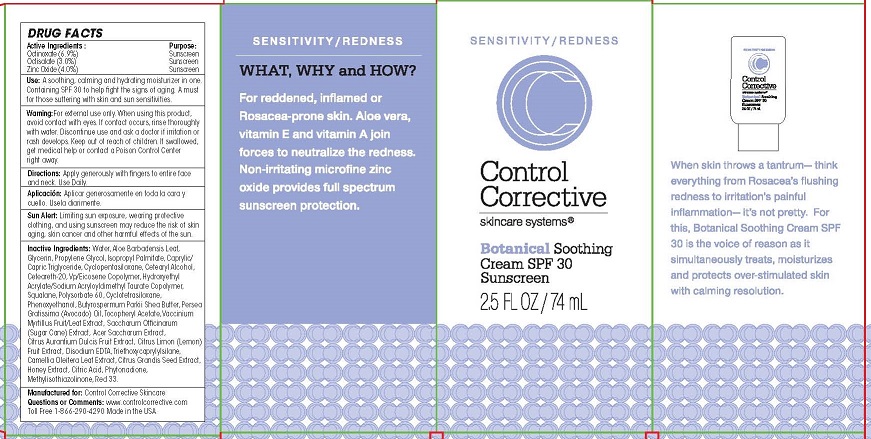 DRUG LABEL: BOTANICAL SOOTHING
NDC: 70764-201 | Form: CREAM
Manufacturer: CONTROL CORRECTIVE SKINCARE INC
Category: otc | Type: HUMAN OTC DRUG LABEL
Date: 20251231

ACTIVE INGREDIENTS: OCTINOXATE 6.9 g/100 mL; OCTISALATE 3 g/100 mL; ZINC OXIDE 4 g/100 mL
INACTIVE INGREDIENTS: WATER; ALOE VERA LEAF; GLYCERIN; PROPYLENE GLYCOL; ISOPROPYL PALMITATE; MEDIUM-CHAIN TRIGLYCERIDES; CYCLOMETHICONE 5; CETOSTEARYL ALCOHOL; POLYOXYL 20 CETOSTEARYL ETHER; VINYLPYRROLIDONE/EICOSENE COPOLYMER; HYDROXYETHYL ACRYLATE/SODIUM ACRYLOYLDIMETHYL TAURATE COPOLYMER (45000 MPA.S AT 1%); SQUALANE; POLYSORBATE 60; CYCLOMETHICONE 4; PHENOXYETHANOL; SHEA BUTTER; AVOCADO OIL; .ALPHA.-TOCOPHEROL ACETATE; VACCINIUM MYRTILLUS WHOLE; ACER SACCHARUM WHOLE; CITRUS AURANTIUM FRUIT; CITRUS LIMON WHOLE; EDETATE DISODIUM; TRIETHOXYCAPRYLYLSILANE; CAMELLIA OLEIFERA LEAF; CITRUS MAXIMA SEED; HONEY; ANHYDROUS CITRIC ACID; PHYTONADIONE; METHYLISOTHIAZOLINONE; D&C RED NO. 33

CONTROL CORRECTIVE - BOTANICAL SOOTHING (70764-201)

ACTIVE INGREDIENTS

OCTINOXATE (6.9%)

OCTISALATE (3.0%)

ZINC OXIDE (4.0%)

PURPOSE

SUNSCREEN

USE

A SOOTHING, CALMING AND HYDRATING MOISTURIZER IN ONE. ALSO HELPS TO REDUCE THE APPEARANCE OF SKIN FLUSHING, REDNESS AND VASCULAR STIMULATION. CONTAINING SPF 30 TO FIGHT THE SIGNES OF AGING. A MUST FOR THOSE SUFFERING WITH SKIN AND SUN SENSITIVITIES.

WARNING

FOR EXTERNAL USE ONLY. WHEN USING THIS PRODUCT, AVOID CONTACT WITH EYES. IF CONTACT OCCURS, RINSE THOROUGHLY WITH WATER. DISCONTINUE USE AND ASK A DOCTOR IF IRRITATION OR RASH DEVELOPS.

DIRECTIONS

APPLY GENEROUSLY WITH FINGERS TO ENTIRE FACE AND NECK. USE DAILY.

OTHER SAFETY INFORMATION

SUN ALERT: LIMITING SUN EXPOSURE, WEARING PROTECTIVE CLOTHING, AND USING SUNSCREEN MAY REDUCE THE RISK OF SKIN AGING, SKIN CANCER, AND OTHER HARMFUL EFFECTS OF THE SUN.

INACTIVE INGREDIENTS

WATER, ALOE BARBADENSIS LEAF, GLYCERIN, PROPYLENE GLYCOL, ISOPROPYL PALMITATE, CAPRYLIC/CAPRIC TRIGLYCERIDES, CYCLOPENTASILOXANE, CETEARYL ALCOHOL, CETEARETH-20, VP/EICOSENE COPOLYMER, SQUALANE, POLYSORBATE 60, CYCLOTETRASILOXANE, PHENOXYETHANOL, BUTYROSPERMUM PARKII BUTTER, PERSEA GRATISSIMA (AVOCADO) OIL, TOCOPHERYL ACETATE, VACCINIUM MYRTILLUS FRUIT/LEAF EXTRACT, SACCHARUM OFFICINARIUM (SUGAR CANE) EXTRACT, ACER SACCHARUM EXTRACT, CITRUS AURANTIUM DULCIS FRUIT EXTRACT, CITRUS LIMON (LEMON) FRUIT EXTRACT, CITRUS GRANDIS SEED EXTRACT, HONEY EXTRACT, CITRIC ACID, PHYTONADIONE, METHYLISOTHIAZOLINONE, RED 33.

KEEP OUT OF REACH OF CHILDREN. IF SWALLOWED, GET MEDICAL HELP OR CONTACT A POISON CONTROL CENTER RIGHT AWAY.

QUESTIONS OR COMMENTS

WWW.CONTROLCORRECTIVE.COM

TOLL FREE 1-866-290-4290 MADE IN USA